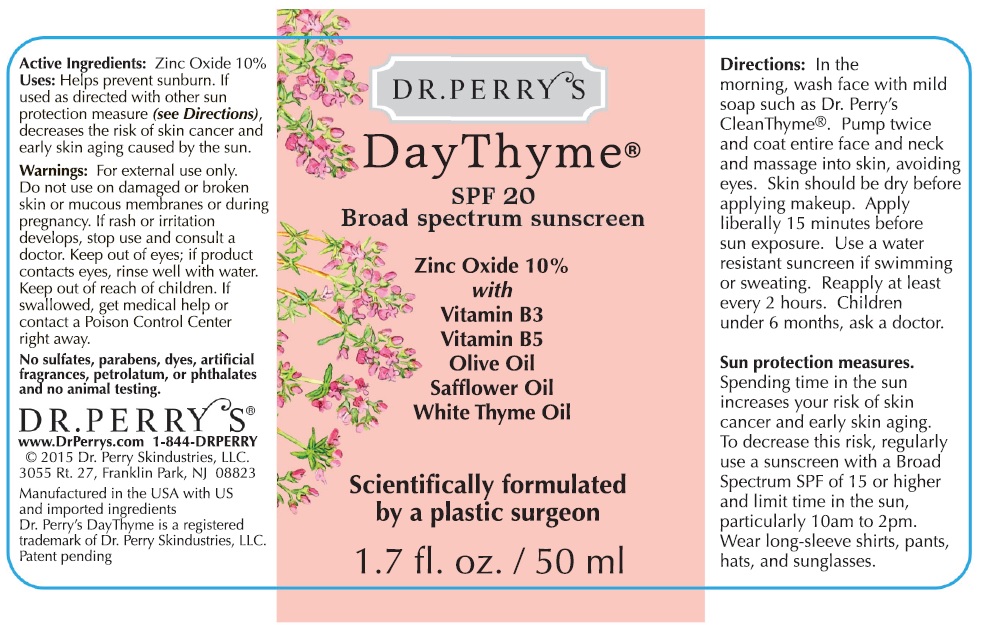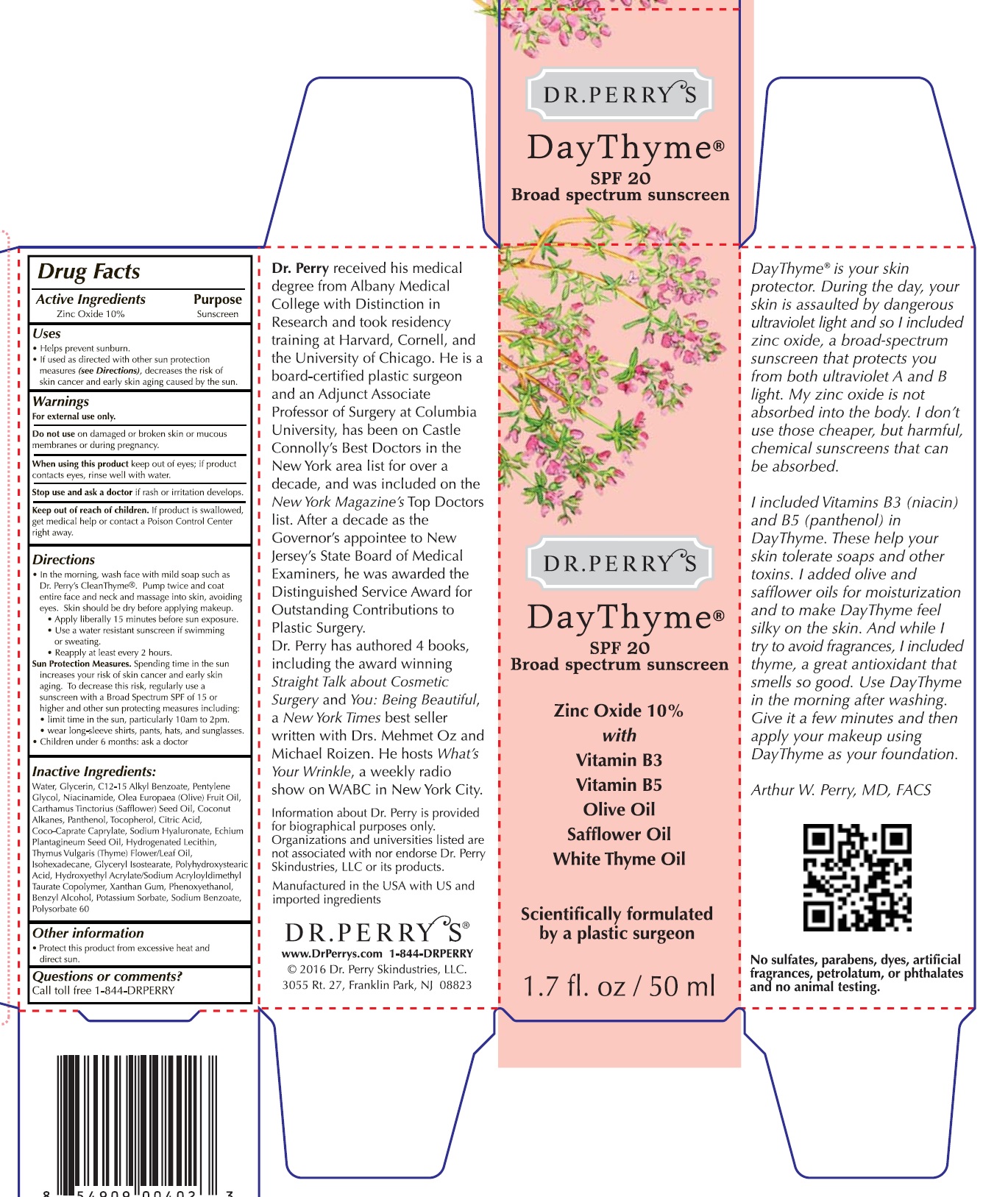 DRUG LABEL: Dr. Perrys Day Thyme SPF 20 Broad Spectrum Sunscreen
NDC: 14268-017 | Form: GEL
Manufacturer: Englewood Lab, Inc.
Category: otc | Type: HUMAN OTC DRUG LABEL
Date: 20231212

ACTIVE INGREDIENTS: ZINC OXIDE 100 mg/1 mL
INACTIVE INGREDIENTS: WATER; GLYCERIN; ALKYL (C12-15) BENZOATE; PENTYLENE GLYCOL; NIACINAMIDE; OLIVE OIL; SAFFLOWER OIL; COCONUT ALKANES; PANTHENOL; TOCOPHEROL; CITRIC ACID MONOHYDRATE; HYALURONATE SODIUM; ECHIUM PLANTAGINEUM SEED OIL; HYDROGENATED SOYBEAN LECITHIN; THYME OIL; ISOHEXADECANE; GLYCERYL ISOSTEARATE; XANTHAN GUM; PHENOXYETHANOL; BENZYL ALCOHOL; POTASSIUM SORBATE; SODIUM BENZOATE; POLYSORBATE 60

Dr. Perry's Day Thyme SPF 20 Broad Spectrum Sunscreen

Active Ingredients

Zinc Oxide 10%

Purpose

Sunscreen

Uses

- Helps prevent sunburn.
- If used as directed with other sun protection measures (), decreases the risk of skin cancer and early sking aging caused by the sun. see Directions

Warnings

For external use only.

Do not use

on damaged or broken skin or mucous membranes or during pregnancy.

When using this product

keep out of eyes; if product contact eyes, rinse well with water.

Stop use and ask a doctor

if rash or irritation develops.

Keep out of reach of children.

If product is swallowed, get medical help or contact a Poison Control Center right away.

Directions

- In the morning, wash face with mild soap such as Dr. Perry's Clean Thyme. Pump twice and coat entire face and neck and massage into skin, avoiding eyes. Skin should be dry before applying makeup.
- Apply liberally 15 minutes before sun exposure.
- Use a water resistant sunscreen if swimming or sweating.
- Reapply at least every 2 hours.
- Spending time in the sun increases your risk of skin cancer and early skin aging. To decrease this risk, regularly use a sunscreen with a Broad Spectrum SPF of 15 or higher and other sun protection measures including: Sun Protection Measures.
- limit time in the sun, particularly between 10 am and 2 pm.
- wear long-sleeve shirts, pants, hats, and sunglasses.
- Children under 6 months: ask a doctor

Inacctive Ingredients:

Water, Glycerin, C12-15 Alkyl Benzoate, Pentylene Glycol, Niacinamide, Olea Europaea (Olive) Fruit Oil, Carthamus Tinctorius (Safflower) Seed Oil, Coconut Alkanes, Panthenol, Tocopherol, Citric Acid, Coco-Caprate Caprylate, Sodium Hyaluronate, Echium Plantagineum Seed Oil, Hydrogenated Lecithin, Thymus Vulgaris (Thyme) Flower/Leaf Oil, Isohexadecane, Glyceryl Isostearate, Polyhydroxystearic Acid, Hydroxyethyl Acrylate/Sodium Acryloyldimethyl Taurate Copolymer, Xanthan Gum, Phenoxyethanol, Benzyl Alcohol, Potassium Sorbate, Sodium Benzoate, Polysorbate 60

Other information

- Protect this product from excessive heat and direct sun.

Questions or comments?

Call toll free 1-844-DRPERRY